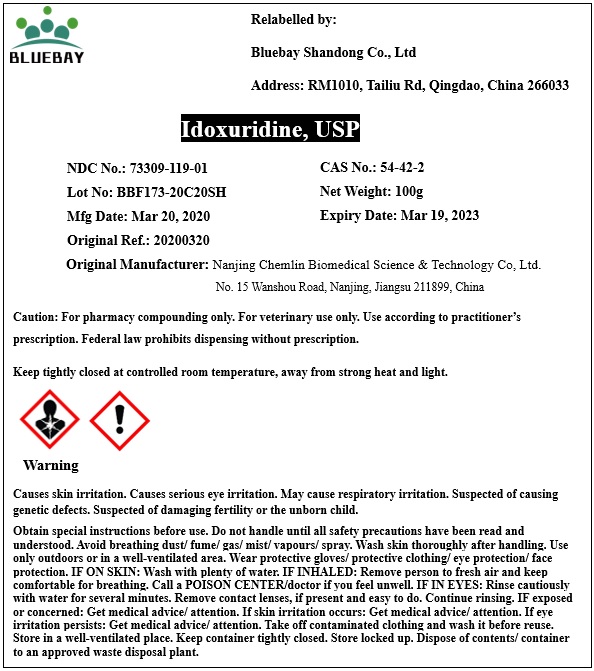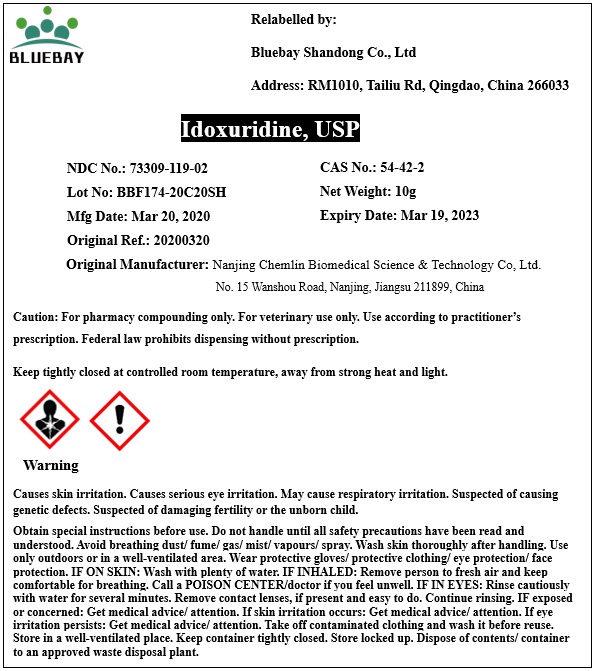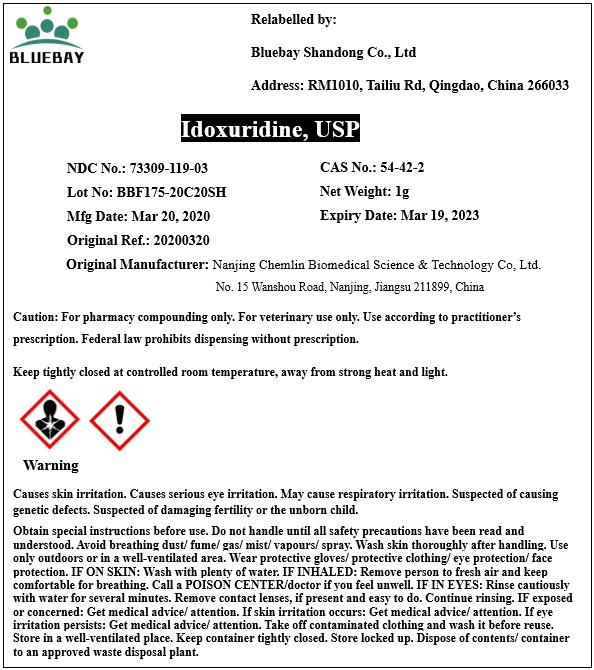 DRUG LABEL: Idoxuridine
NDC: 73309-119 | Form: POWDER
Manufacturer: BLUEBAY SHANDONG CO.,LTD
Category: other | Type: BULK INGREDIENT
Date: 20200414

ACTIVE INGREDIENTS: IDOXURIDINE 1 g/1 g

Idoxuridine